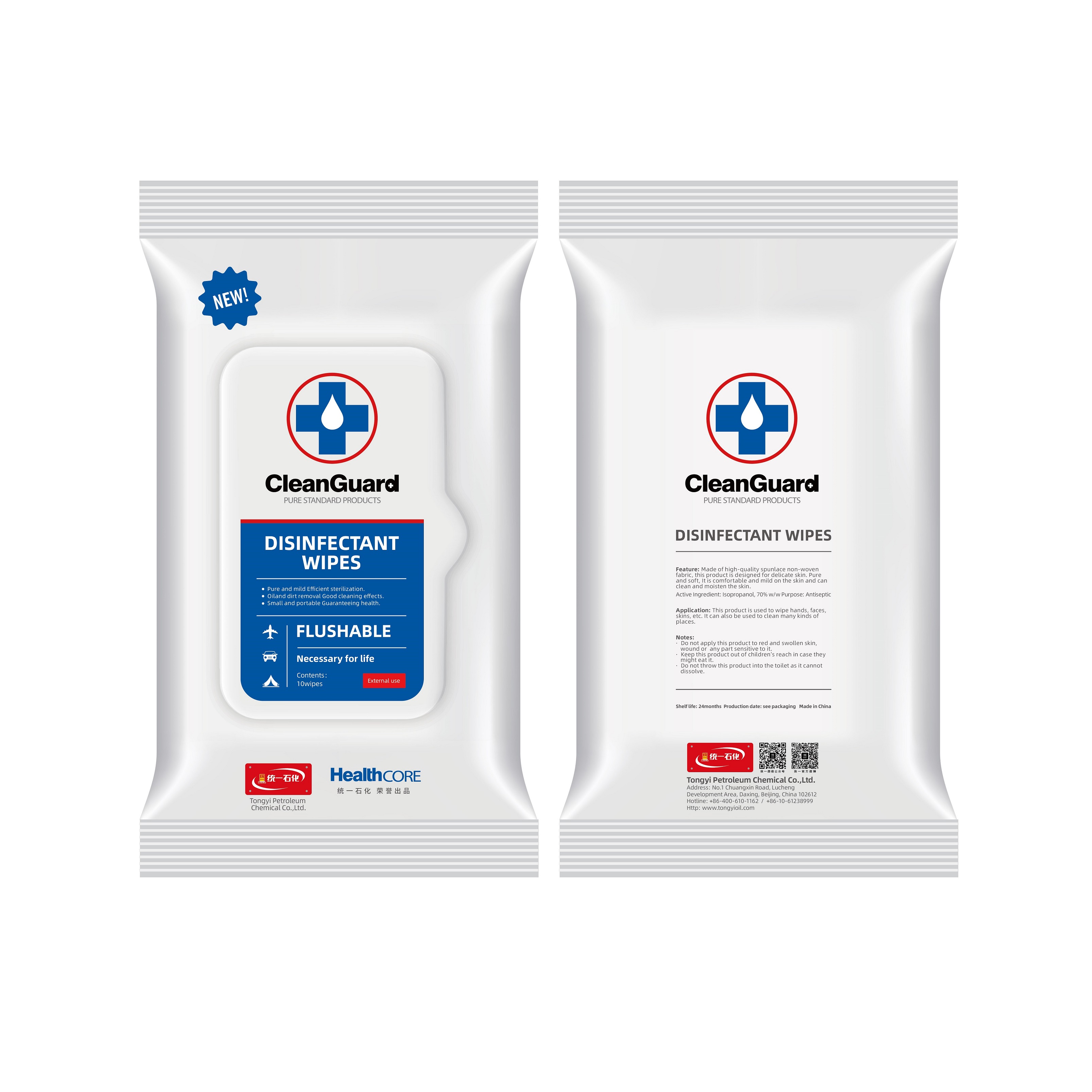 DRUG LABEL: TongYi CleanGuard Disinfectant Wipes
NDC: 73681-5561 | Form: CLOTH
Manufacturer: Tongyi Petroleum Chemical Co., Ltd.
Category: otc | Type: HUMAN OTC DRUG LABEL
Date: 20200918

ACTIVE INGREDIENTS: ISOPROPYL ALCOHOL 70 1/100 1
INACTIVE INGREDIENTS: WATER 30 1/100 1

TongYi, Disinfectant Wipes, *10, R2

Active ingredient

Isopropanol 70% w/w, Purpose: Antiseptic

Inactive ingredient

Water

Purpose

Antiseptic.

This product is used to wipe hands, faces, skins, etc. It can also be used to clean many kinds of places.

When using

This product is used to wipe hands, faces, skins, etc. It can also be used to clean many kinds of places.

Do not use

Use only as directed.
Do not use for cases not directed.

Stop use

Stop use if the product's volatile gases cause discomfort, or if you experience respiratory irritation such as cough, asthma, or difficulty breathing.

Ask doctor

If using the product causes serious discomfort, ask or see your doctor.

Ask doctor/pharmacist

If using the product causes serious discomfort, ask or see your doctor/pharmacist.

Keep out of reach of children

Questions

Please contact with us at the phone number +86-10-61238999 when you have any questions.

Pregnancy or breast feeding

Pregnant or breast feeding women shall follow doctor advice.

Indications & usage

This product is used to wipe hands, faces, skins, etc. It can also be used to clean many kinds of places.

Dosage & administration

Use it as needed, after following the usage instructions.

For external use only.

Dosage forms & strengths

This product is liquid dosage form.
The active ingredient strength is 70%.

Warnings

Do not apply this product to red and swollen skin, wound or any part sensitive to it.
Keep this product out of children’s reach in case they might eat it.
Do not throw this product into the toilet as it cannot dissolve.